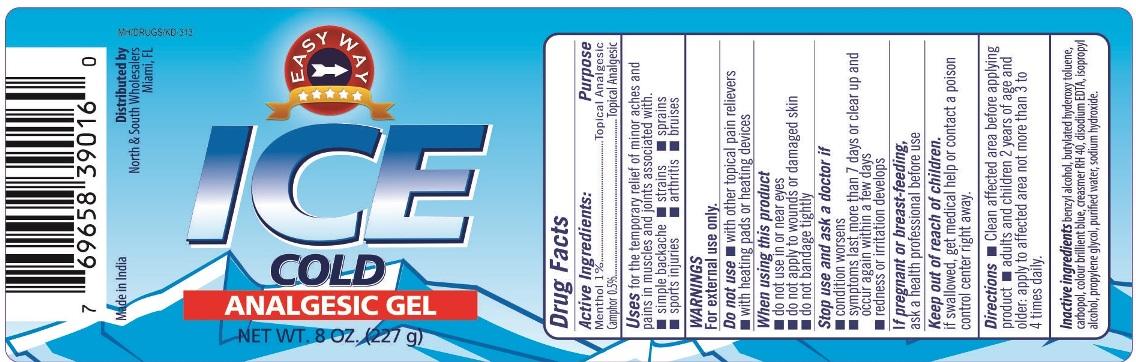 DRUG LABEL: Ice Cold Analgesic
NDC: 70201-003 | Form: GEL
Manufacturer: North & South Wholesalers LLC
Category: otc | Type: HUMAN OTC DRUG LABEL
Date: 20151109

ACTIVE INGREDIENTS: MENTHOL 1 g/100 g; CAMPHOR (SYNTHETIC) 0.5 g/100 g
INACTIVE INGREDIENTS: BENZYL ALCOHOL; BUTYLATED HYDROXYTOLUENE; CARBOMER HOMOPOLYMER TYPE B (ALLYL SUCROSE CROSSLINKED); BRILLANT BLUE; POLYOXYL 40 HYDROGENATED CASTOR OIL; EDETATE DISODIUM; ISOPROPYL ALCOHOL; PROPYLENE GLYCOL; WATER; SODIUM HYDROXIDE

Ice Cold Analgesic Gel

Active Ingredients

Menthol 1%

Camphor 0.5%

Purpose

Topical Analgesic

Uses

for the temporary relief of minor aches and pains in muscles and joints associated with:

- simple backache
- strains
- sprains
- sports injuries
- arthritis
- bruises

Warnings

For external use only

Do not use

- with other topical pain relievers
- with heating pads or heating devices

When using this product

- do not use in or near eyes
- do not apply to wounds or damaged skin
- do not bandage tightly

Stop use and ask a doctor if

- condition worsens
- symptoms last more than 7 days or clean up and occur again within a few days
- redness or irritation develops

PREGNANCY OR BREAST FEEDING

If pregnant or breast-feeding, ask a health professional before use

Keep out of the reach of children

If swallowed, get medical help or contact a poison control center right away

Directions

- clean affected area before applying product
- adults and children 2 years of age and older: apply to affected area not more than 3 to 4 times daily

Inactive Ingredients

benzyl alcohol, butylated hydroxy toluene, carbopol, color brilient blue, creasmer RH-40, disodium EDTA, isopropyl alcohol, propylene glycol, purified water, sodium hydroxide.

PACKAGE LABEL

PRINCIPAL DISPLAY PANEL

ICE COLD ANALGESIC GEL

Topical Analgesic

NET WT.8 OZ (227g)